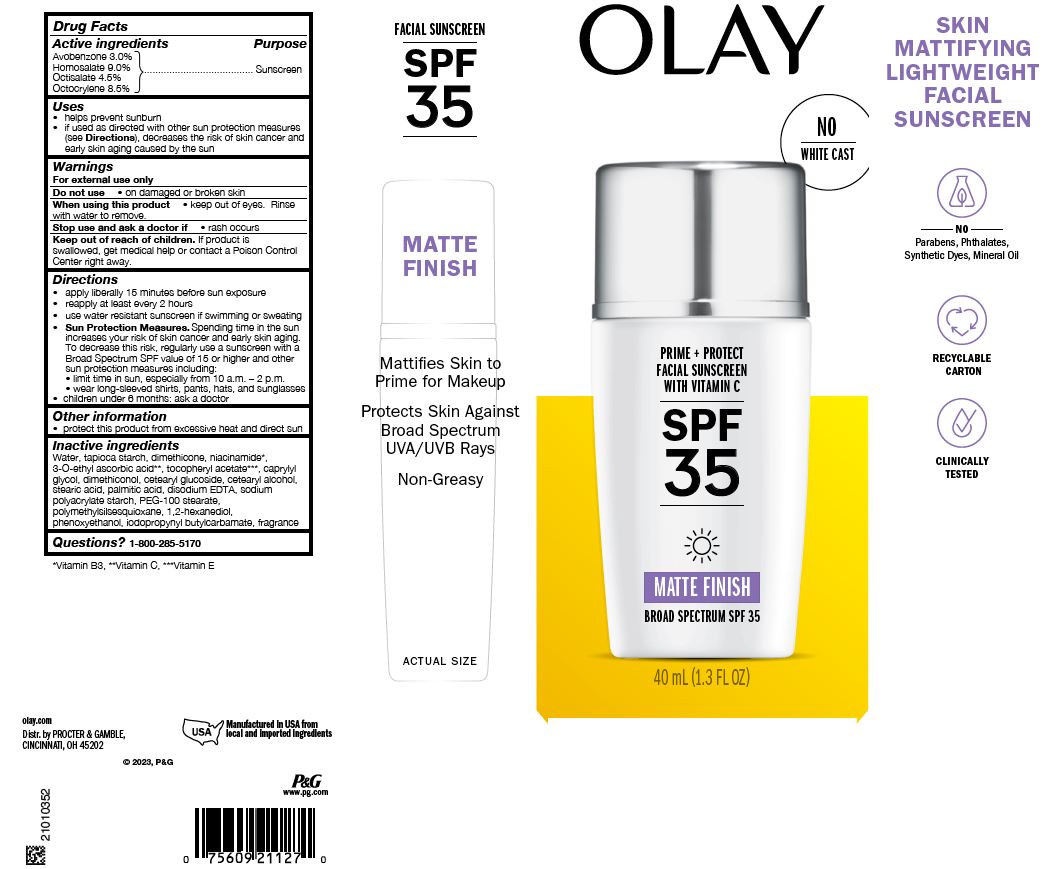 DRUG LABEL: OLAY Prime plus Protect Facial Sunscreen with Vitamin C SPF35 Matte Finish
NDC: 69423-742 | Form: LOTION
Manufacturer: The Procter & Gamble Manufacturing Company
Category: otc | Type: HUMAN OTC DRUG LABEL
Date: 20251218

ACTIVE INGREDIENTS: AVOBENZONE 3 g/100 mL; HOMOSALATE 9 g/100 mL; OCTISALATE 4.5 g/100 mL; OCTOCRYLENE 8.5 g/100 mL
INACTIVE INGREDIENTS: DIMETHICONOL (50000 CST); POLYMETHYLSILSESQUIOXANE (4.5 MICRONS); WATER; 1,2-HEXANEDIOL; PHENOXYETHANOL; CAPRYLYL GLYCOL; DIMETHICONE; NIACINAMIDE; .ALPHA.-TOCOPHEROL ACETATE; CETEARYL GLUCOSIDE; CETOSTEARYL ALCOHOL; 3-O-ETHYL ASCORBIC ACID; STEARIC ACID; EDETATE DISODIUM; PEG-100 STEARATE; PALMITIC ACID; STARCH, TAPIOCA

OLAY Prime plus Protect Facial Sunscreen with Vitamin C SPF35 Matte Finish

Drug Facts

ACTIVE INGREDIENT

Avobenzone 3.0%
Homosalate 4.0%
Octisalate 4.5%
Octocrylene 2.6%

PURPOSE

Sunscreen

Uses

- helps prevent sunburn
- if used as directed with other sun protection measures (see Directions), decreases the risk of skin cancer and early skin aging caused by the sun

Warnings

For external use only

Do not use on damaged or broken skin

When using this product keep out of eyes. Rinse with water to remove.

Stop use and ask a doctor if rash occurs

Keep out of reach of children. If product is swallowed, get medical help or contact a Poison Control Center right away.

Directions

- apply liberally 15 minutes before sun exposure
- reapply at least every 2 hours
- use water resistant sunscreen if swimming or sweating
- Sun Protection Measures. Spending time in the sun increases your risk of skin cancer and early skin aging. To decrease this risk, regularly use a sunscreen with a Broad Spectrum SPF value of 15 or higher and other sun protection measures including:
  - limit time in sun, especially from 10 a.m. – 2 p.m.
  - wear long-sleeved shirts, pants, hats, and sunglasses
- children under 6 months: ask a doctor

Other information

- protect this product from excessive heat and direct sun

Inactive ingredients

Water, tapioca starch, dimethicone, niacinamide*, 3-O-ethyl ascorbic acid**, tocopheryl acetate***, caprylyl glycol, dimethiconol, cetearyl glucoside, cetearyl alcohol, stearic acid, palmitic acid, disodium EDTA, sodium polyacrylate starch, PEG-100 stearate, polymethylsilsesquioxane, 1,2-hexanediol, phenoxyethanol, iodopropynyl butylcarbamate, fragrance

Questions or comments?

Call 1-800-285-5170

Dist. by PROCTER & GAMBLE,
CINCINNATI, OH 45202

PRINCIPAL DISPLAY PANEL - 1.3 fl oz Carton

OLAY

Prime + Protect

Facial Sunscreen with Vitamin C

SPF35

Matte Finish

BROAD SPECTRUM SPF 35

40 mL (1.3 FL OZ)